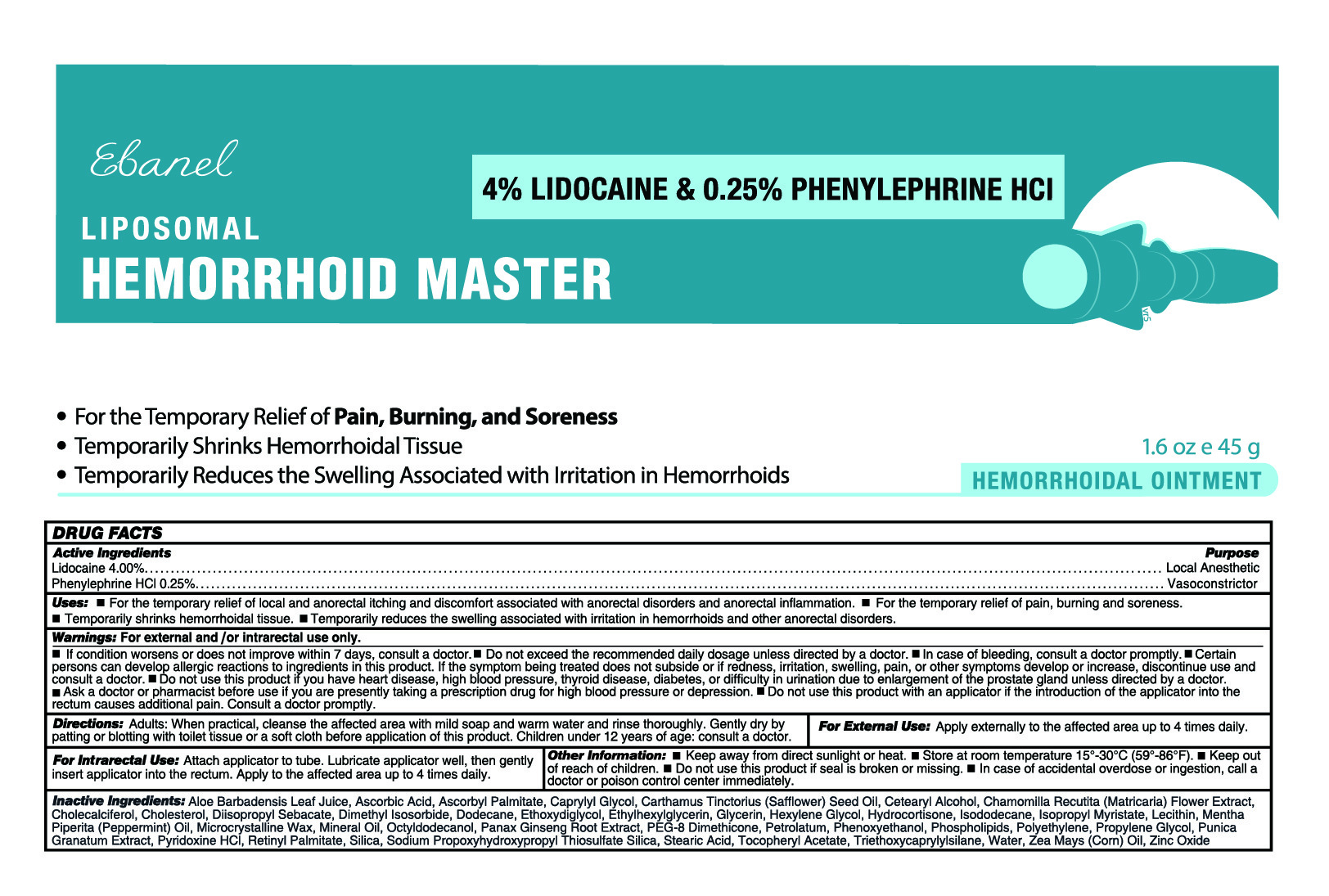 DRUG LABEL: Hemorrhoid Master
NDC: 63742-045 | Form: OINTMENT
Manufacturer: Clinical Resolution Laboratory, Inc.
Category: otc | Type: HUMAN OTC DRUG LABEL
Date: 20250604

ACTIVE INGREDIENTS: LIDOCAINE 4 mg/1 g; PHENYLEPHRINE HYDROCHLORIDE 2.5 mg/1 g
INACTIVE INGREDIENTS: ETHYLHEXYLGLYCERIN; GLYCERIN; PETROLATUM; LECITHIN, SOYBEAN; MINERAL OIL; ALOE BARBADENSIS LEAF JUICE; ASCORBIC ACID; HYDROCORTISONE; WATER; ZEA MAYS (CORN) OIL; ISOPROPYL MYRISTATE; MENTHA PIPERITA (PEPPERMINT) OIL; PANAX GINSENG ROOT; SILICA; CHOLECALCIFEROL, (5E)-; DIMETHYL ISOSORBIDE; DODECANE; ETHOXYDIGLYCOL; HEXYLENE GLYCOL; PEG-8 DIMETHICONE; PHENOXYETHANOL; EGG PHOSPHOLIPIDS; POLYETHYLENE; PROPYLENE GLYCOL; RETINYL PALMITATE; TRIETHOXYCAPRYLYLSILANE; ZINC OXIDE; ISODODECANE; ASCORBYL PALMITATE; MICROCRYSTALLINE WAX; OCTYLDODECANOL; POMEGRANATE; PYRIDOXINE HCL; SODIUM PROPOXYHYDROXYPROPYL THIOSULFATE SILICA; STEARIC ACID; .ALPHA.-TOCOPHEROL ACETATE, D-; CAPRYLYL GLYCOL; CHAMOMILE; CARTHAMUS TINCTORIUS (SAFFLOWER) SEED OIL; CETEARYL ALCOHOL; CHOLESTEROL; DIISOPROPYL SEBACATE

Active Ingredients

Lidocaine 4.00%

Phenylephrine HCl 0.25%

Directions

■ Adults: When practical, cleanse the affected area with mild soap and warm water and rinse thoroughly. Gently dry by patting or blotting with toilet tissue or a soft cloth before application of this product. Children under 12 years of age: consult a doctor.

■ For External Use: Apply externally to the affected area up to 4 times daily.

■ For Intrarectal use: Attach applicator to tube. Lubricate applicator well, then gently insert applicator into the rectum. Apply to the affected area up to 4 times daily.

Warnings: For external and/ or intrarectal use only.

■ If condition worsens or does not improve within 7 days, consult a doctor.

■ Do not exceed the recommended daily dosage unless directed by a doctor.

■ In case of bleeding, consult a doctor promptly.

■ Certain persons can develop allergic reactions to ingredients in this product. If the symptom being treated does not subside or if redness, irritation, swelling, pain, or other symptoms develop or increase, discontinue use and consult a doctor.

■ Do not use this product if you have heart disease, high blood pressure, thyroid disease, diabetes, or difficulty in urination due to enlargement of the prostate gland unless directed by a doctor.

■ Ask a doctor or pharmacist before use if you are presently taking a prescription drug for high blood pressure or depression.

■ Do not use this product with an applicator if the introduction of the applicator into the rectum causes additional pain. Consult a doctor promptly.

Uses

■ For the temporary relief of local and anorectal itching and discomfort associated with anorectal disorders and anorectal inflammation.

■ For the temporary relief of pain, burning and soreness.

■ Temporarily shrinks hemorrhoidal tissue.

■ Temporarily reduces the swelling associated with irritation in hemorrhoids and other anorectal disorders.

KEEP OUT OF REACH OF CHILDREN

■ Adults: When practical, cleanse the affected area with mild soap and warm water and rinse thoroughly. Gently dry by patting or blotting with toilet tissue or a soft cloth before application of this product. Children under 12 years of age: consult a doctor.

■ For External Use: Apply externally to the affected area up to 4 times daily.

■ For Intrarectal use: Attach applicator to tube. Lubricate applicator well, then gently insert applicator into the rectum. Apply to the affected area up to 4 times daily.

Inactive Ingredients

Aloe Barbadensis Leaf Juice, Ascorbic Acid, Ascorbyl Palmitate, Caprylyl Glycol, Carthamus Tinctorius (Safflower) Seed Oil, Cetearyl Alcohol, Chamomilla Recutita (Matricaria) Flower Extract, Cholecalciferol, Cholesterol, Diisopropyl Sebacate, Dimethyl Isosorbide, Dodecane, Ethoxydiglycol, Ethylhexylglycerin, Glycerin, Hexylene Glycol, Hydrocortisone, Isododecane, Isopropyl Myristate, Lecithin, Mentha Piperita (Peppermint) Oil, Microcrystalline Wax, Mineral Oil, Octyldodecanol, Panax Ginseng Root Extract, PEG-8 Dimethicone, Petrolatum, Phenoxyethanol, Phospholipids, Polyethylene, Propylene Glycol, Punica Granatum Extract, Pyridoxine HCl, Retinyl Palmitate, Silica, Sodium Propoxyhydroxypropyl Thiosulfate Silica, Stearic Acid, Tocopheryl Acetate, Triethoxycaprylylsilane, Water, Zea Mays (Corn) Oil, Zinc Oxide

Purpose

Local Anesthetic

Vasoconstrictor

Other Information

■ Keep away from direct sunlight or heat.

■ Store at room temperature 15°-30°C (59°-86°F).

■ Keep out of reach of children.

■ In case of accidental overdose or ingestion, call a doctor or poison control center immediately.

■ Do not use this product if seal is broken or missing.